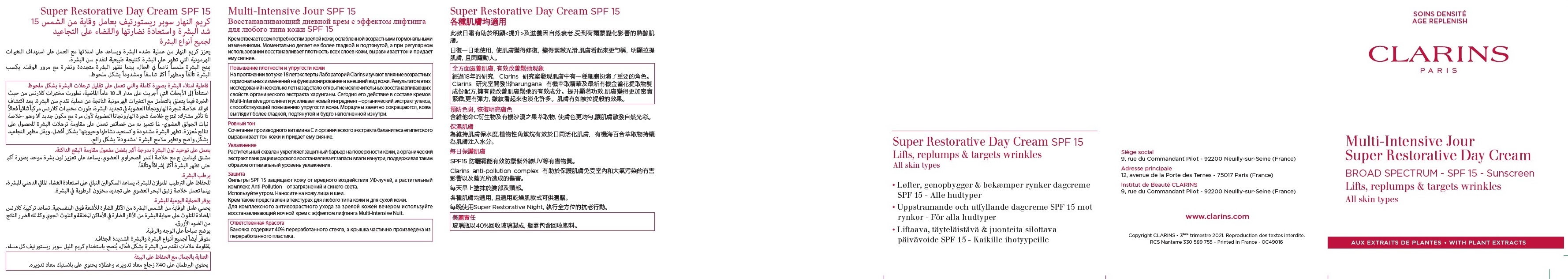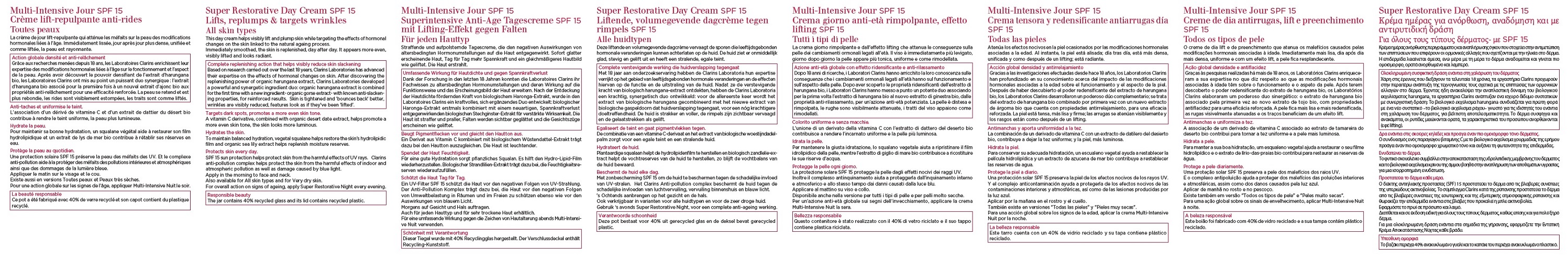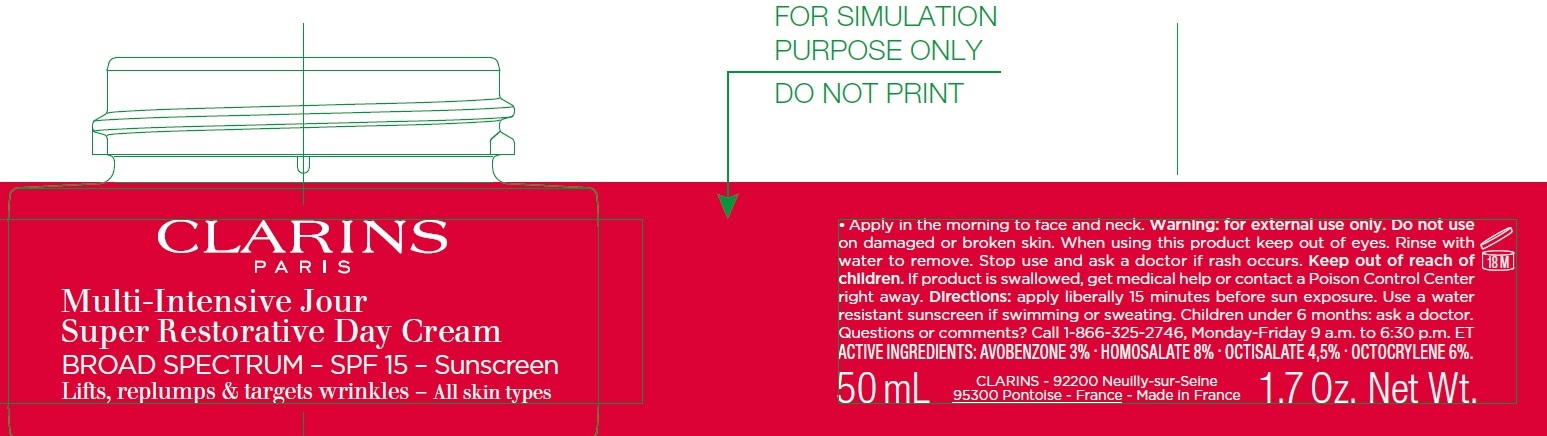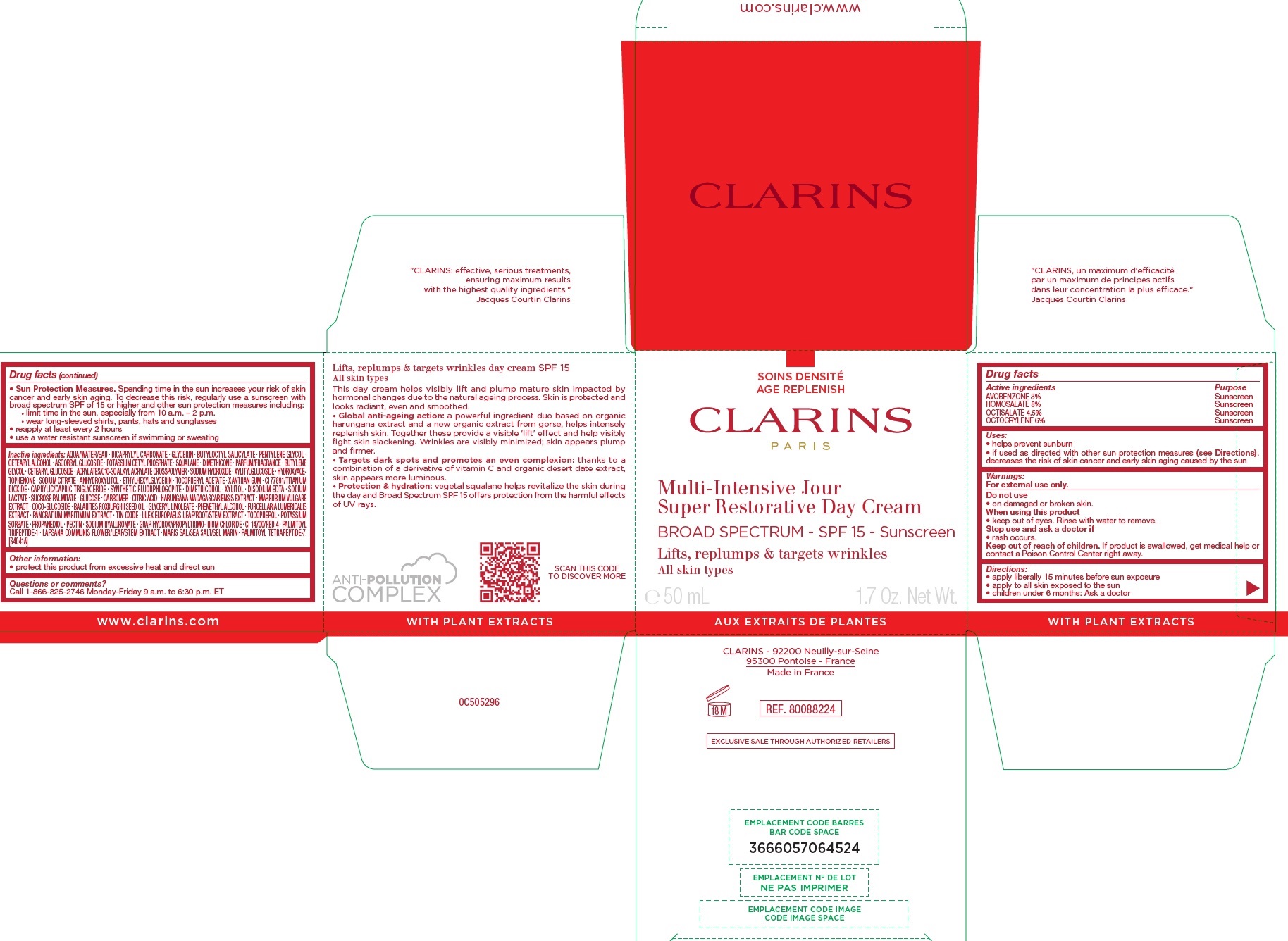 DRUG LABEL: CLARINS - MULTI-INTENSIVE JOUR SUPER RESTORATIVE DAY BROAD SPECTRUM - SPF 15 - SUNSCREEN
NDC: 58668-9920 | Form: CREAM
Manufacturer: Laboratoires Clarins
Category: otc | Type: HUMAN OTC DRUG LABEL
Date: 20250506

ACTIVE INGREDIENTS: AVOBENZONE 30 mg/1 mL; HOMOSALATE 80 mg/1 mL; OCTISALATE 45 mg/1 mL; OCTOCRYLENE 60 mg/1 mL
INACTIVE INGREDIENTS: WATER; DICAPRYLYL CARBONATE; GLYCERIN; BUTYLOCTYL SALICYLATE; PENTYLENE GLYCOL; CETOSTEARYL ALCOHOL; ASCORBYL GLUCOSIDE; POTASSIUM CETYL PHOSPHATE; SQUALANE; DIMETHICONE; BUTYLENE GLYCOL; CETEARYL GLUCOSIDE; SODIUM HYDROXIDE; XYLITYLGLUCOSIDE; HYDROXYACETOPHENONE; SODIUM CITRATE; ANHYDROXYLITOL; ETHYLHEXYLGLYCERIN; .ALPHA.-TOCOPHEROL ACETATE; XANTHAN GUM; TITANIUM DIOXIDE; MEDIUM-CHAIN TRIGLYCERIDES; MAGNESIUM POTASSIUM ALUMINOSILICATE FLUORIDE; XYLITOL; EDETATE DISODIUM ANHYDROUS; SODIUM LACTATE; SUCROSE PALMITATE; ANHYDROUS DEXTROSE; CARBOMER HOMOPOLYMER, UNSPECIFIED TYPE; CITRIC ACID MONOHYDRATE; HOREHOUND; COCO GLUCOSIDE; BALANITES ROXBURGHII SEED OIL; GLYCERYL LINOLEATE; PHENYLETHYL ALCOHOL; FURCELLERAN; STANNIC OXIDE; TOCOPHEROL; POTASSIUM SORBATE; PROPANEDIOL; PECTIN; HYALURONATE SODIUM; FD&C RED NO. 4; PALMITOYL TRIPEPTIDE-1; LAPSANA COMMUNIS FLOWERING TOP; PALMITOYL TETRAPEPTIDE-7

CLARINS – MULTI-INTENSIVE JOUR / SUPER RESTORATIVE DAY CREAM BROAD SPECTRUM – SPF 15 - SUNSCREEN

Active ingredients

AVOBENZONE 3%

HOMOSALATE 8%

OCTISALATE 4.5%

OCTOCRYLENE 6%

Purpose

Sunscreen

Uses:

• helps prevent sunburn • if used as directed with other sun protection measures (see), decreases the risk of skin cancer and early skin aging caused by the sun
Directions

Warnings:

For external use only.

Do not use

• on damaged or broken skin.

When using this product

• keep out of eyes. Rinse with water to remove.

Stop use and ask a doctor if

• rash occurs.

Keep out of reach of children.

If product is swallowed, get me dical help or contact a Poison Control Center right away.

Directions:

• apply liberally 15 minutes before sun exposure • apply to all skin exposed to the sun • children under 6 months: Ask a doctor

• Spending time in the sun in creases your risk of skin cancer and early skin aging. To decrease this risk, regularly use a sunscreen with broad spectrum SPF of 15 or higher and other sun protection measures including: • limit time in the sun, especially from 10 a.m. – 2 p.m. • wear long-sleeved shirts, pants, hats and sunglasses • reapply at least every 2 hours • use a water resistant sun screen if swimming or sweating Sun Protection Measures.

Inactive ingredients:

AQUA/WATER/EAU . DICAPRYLYL CARBONATE . GLYCERIN . BUTYLOCTYL SALICYLATE . PENTYLENE GLYCOL . CETEARYL ALCOHOL . ASCORBYL GLUCOSIDE . POTASSIUM CETYL PHOSPHATE . SQUALANE . DIMETHICONE . PARFUM/FRAGRANCE . BUTYLENE GLYCOL . CETEARYL GLUCOSIDE . ACRYLATES/C10-30 ALKYL ACRYLATE CROSSPOLYMER . SODIUM HYDROXIDE . XYLITYLGLUCOSIDE . HYDROXYACETOPHENONE . SODIUM CITRATE . ANHYDROXYLITOL . ETHYLHEXYLGLYCERIN . TOCOPHERYL ACETATE . XANTHAN GUM . CI 77891/TITANIUM DIOXIDE . CAPRYLIC/CAPRIC TRIGLYCERIDE . SYNTHETIC FLUORPHLOGOPITE . DIMETHICONOL . XYLITOL . DISODIUM EDTA . SODIUM LACTATE . SUCROSE PALMITATE . GLUCOSE . CARBOMER . CITRIC ACID . HARUNGANA MADAGASCARIENSIS EXTRACT . MARRUBIUM VULGARE EXTRACT . COCO-GLUCOSIDE . BALANITES ROXBURGHII SEED OIL . GLYCERYL LINOLEATE . PHENETHYL ALCOHOL . FURCELLARIA LUMBRICALIS EXTRACT . PANCRATIUM MARITIMUM EXTRACT . TIN OXIDE . ULEX EUROPAEUS LEAF/ROOT/STEM EXTRACT . TOCOPHEROL . POTASSIUM SORBATE . PROPANEDIOL . PECTIN . SODIUM HYALURONATE . GUAR HYDROXYPROPYLTRIMO- NIUM CHLORIDE . CI 14700/RED 4 . PALMITOYL TRIPEPTIDE-1 . LAPSANA COMMUNIS FLOWER/LEAF/STEM EXTRACT . MARIS SAL/SEA SALT/SEL MARIN . PALMITOYL TETRAPEPTIDE-7. [S4041A]

Other information:

• protect this product from excessive heat and direct sun

Questions or comments?

Call 1-866-325-2746 Monday-Friday 9 a.m. to 6:30 p.m. ET